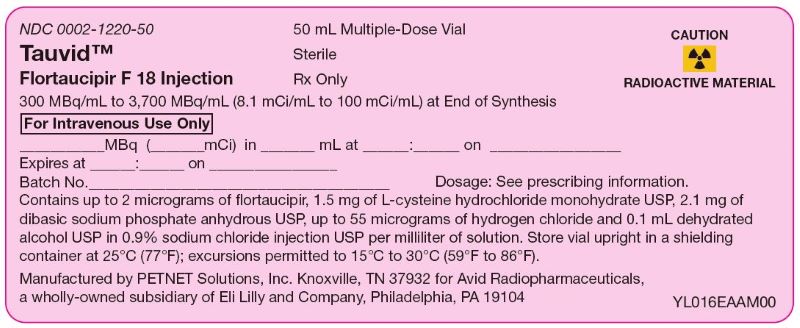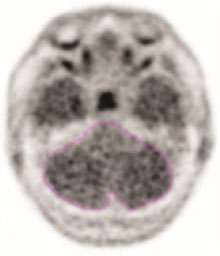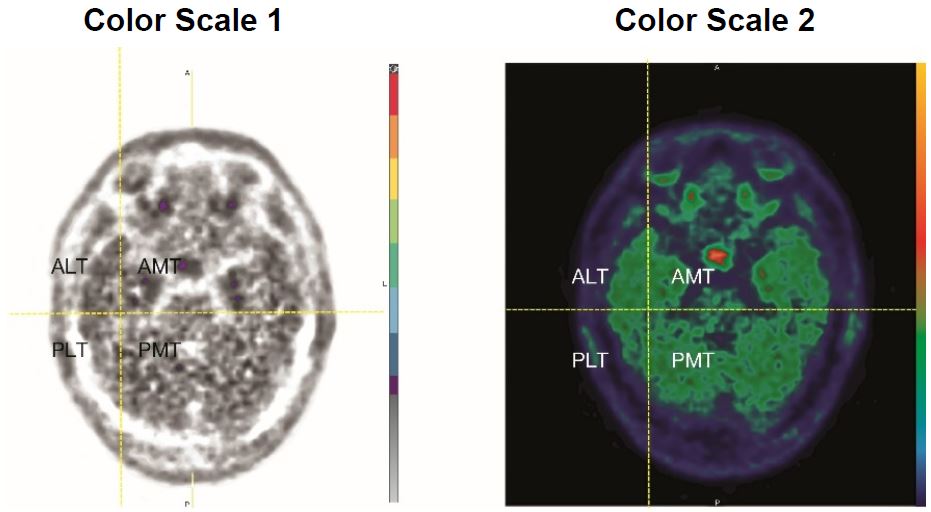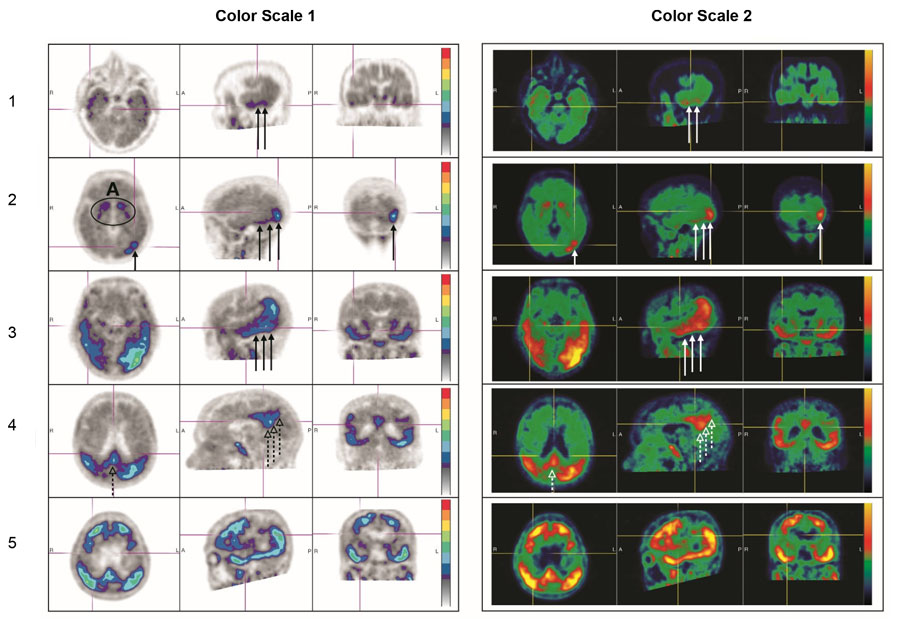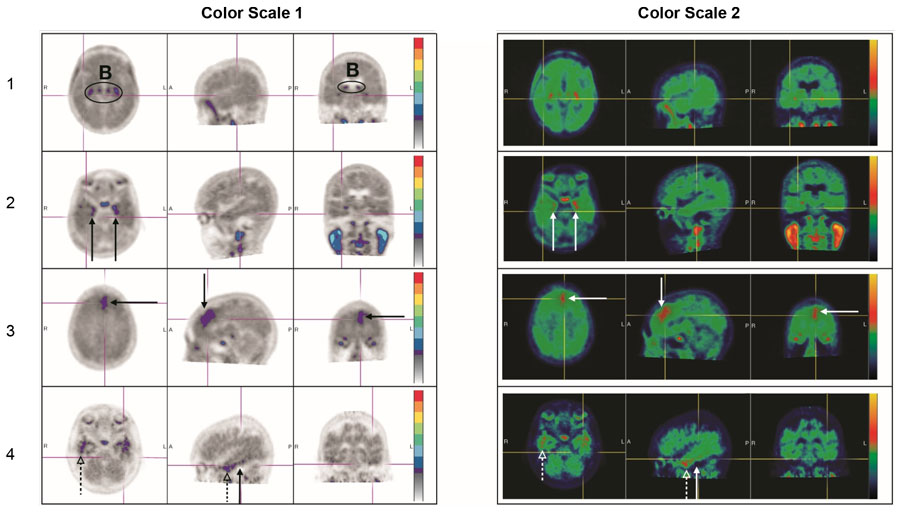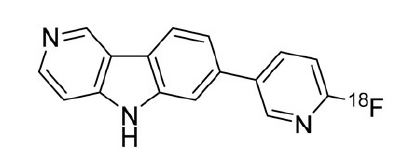 DRUG LABEL: TAUVID
NDC: 0002-1220 | Form: INJECTION, SOLUTION
Manufacturer: Eli Lilly and Company
Category: prescription | Type: HUMAN PRESCRIPTION DRUG LABEL
Date: 20251230

ACTIVE INGREDIENTS: Flortaucipir F-18 100 mCi/1 mL
INACTIVE INGREDIENTS: Cysteine Hydrochloride 1.5 mg/1 mL; Sodium phosphate, Dibasic, Anhydrous 2.1 mg/1 mL; Alcohol 78.9 mg/1 mL; Sodium Chloride 8.1 mg/1 mL; Hydrochloric Acid 55 mg/1 mL

HIGHLIGHTS OF PRESCRIBING INFORMATION

These highlights do not include all the information needed to use TAUVID safely and effectively. See full prescribing information for TAUVID.
TAUVID™ (flortaucipir F 18 injection), for intravenous use
Initial U.S. Approval: 2020

1 INDICATIONS AND USAGE

TAUVID is a radioactive diagnostic agent indicated for positron emission tomography (PET) imaging of the brain to estimate the density and distribution of aggregated tau neurofibrillary tangles (NFTs) in adult patients with cognitive impairment who are being evaluated for Alzheimer's disease (AD). (1)

Limitations of Use

TAUVID is not indicated for use in the evaluation of patients for chronic traumatic encephalopathy (CTE). (1, 5.2)

2 DOSAGE AND ADMINISTRATION

- Recommended dose is 370 MBq (10 mCi), administered as a bolus intravenous injection. (2.2)
- Initiate imaging approximately 80 minutes after drug administration. (2.3)
- See full prescribing information for additional preparation, administration, imaging, and radiation dosimetry information. (2)

3 DOSAGE FORMS AND STRENGTHS

Injection: 300 MBq/mL to 3,700 MBq/mL (8.1 mCi/mL to 100 mCi/mL) of flortaucipir F 18 in a multiple-dose vial. (3)

4 CONTRAINDICATIONS

None. (4)

5 WARNINGS AND PRECAUTIONS

- Risk of Misdiagnosis in Patients Evaluated for Alzheimer's disease: Consider additional evaluation to confirm the absence of AD pathology in patients with a negative TAUVID scan. (2.6, 5.1)
- Risk of Chronic Traumatic Encephalopathy Misdiagnosis: The safety and effectiveness of TAUVID have not been established for patients being evaluated for CTE. (1, 5.2)
- Radiation Risk: Ensure safe drug handling to protect patients and health care workers from unintentional radiation exposure. (2.1, 5.3)

6 ADVERSE REACTIONS

Most common adverse reactions (frequency ≥ 0.5%) were headache, injection site pain, and increased blood pressure. (6.1)

To report SUSPECTED ADVERSE REACTIONS, contact Eli Lilly and Company at 1-800-LillyRx (1-800-545-5979) or FDA at 1-800-FDA-1088 or www.fda.gov/medwatch.

8 USE IN SPECIFIC POPULATIONS

Lactation: Interrupt breastfeeding. Advise a lactating woman to avoid breastfeeding for 4 hours after TAUVID administration. (8.2)

FULL PRESCRIBING INFORMATION

1 INDICATIONS AND USAGE

TAUVID is indicated for use with positron emission tomography (PET) imaging of the brain to estimate the density and distribution of aggregated tau neurofibrillary tangles (NFTs) in adult patients with cognitive impairment who are being evaluated for Alzheimer's disease (AD).

Limitations of Use

TAUVID is not indicated for use in the evaluation of patients for chronic traumatic encephalopathy (CTE) [see Warnings and Precautions (5.2)].

2 DOSAGE AND ADMINISTRATION

2.1 Radiation Safety - Drug Handling

TAUVID is a radioactive drug. Only authorized persons qualified by training and experience should receive, use, and administer TAUVID. Handle TAUVID with appropriate safety measures to minimize radiation exposure during administration [see Warnings and Precautions (5.3)]. Use waterproof gloves and effective shielding, including syringe shields, when preparing and handling TAUVID.

2.2 Recommended Dosage and Administration Instructions

Recommended Dose

The recommended amount of radioactivity to be administered for PET imaging is 370 MBq (10 mCi), administered as an intravenous bolus injection in a total volume of 10 mL or less.

Preparation and Administration

- Assessment of pregnancy status is recommended in females of reproductive potential before administering TAUVID.
- Use aseptic technique and radiation shielding during the preparation and administration of TAUVID [see Dosage and Administration (2.1)].
- Visually inspect the radiopharmaceutical solution prior to administration. Do not use it if it contains particulate matter or if it is discolored (TAUVID is a clear, colorless solution).
- TAUVID may be diluted aseptically with 0.9% Sodium Chloride Injection to a maximum dilution of 1:5 by the end-user. Diluted product should be used within 4 hours of dilution and prior to product expiry.
- Assay the dose in a suitable dose calibrator prior to administration.

Post-Administration Instructions

- Follow the TAUVID injection with an intravenous flush of 0.9% Sodium Chloride injection, USP.
- Dispose of any unused TAUVID in compliance with applicable regulations.

2.3 Image Acquisition

Starting approximately 80 minutes after the TAUVID intravenous injection, obtain a 20-minute PET image with the patient supine. Position the head to center the brain (including the cerebellum) in the PET scanner field of view. Tape or other flexible head restraints may be used to reduce head movement.

2.4 Image Display

The goal of the read is to identify and locate areas of flortaucipir activity in the neocortex that are greater than the background activity (background activity is defined as up to 1.65-fold the measured cerebellar average). For optimal display, select a color scale with a rapid transition between two distinct colors and adjust the scale so that the transition occurs at the 1.65-fold threshold. Examine the posterolateral temporal (PLT), occipital, parietal, and frontal regions bilaterally. Neocortical activity in either hemisphere contributes to image interpretation. Activity in white matter or regions outside the brain does not contribute to image interpretation. To help identify the PLT, consider subdividing the temporal lobe into four quadrants as instructed below. Activity in the anterior and medial temporal lobe does not contribute to image interpretation of a positive TAUVID pattern.

Image Display and Orientation

Display images in the transverse, sagittal, and coronal planes. Reorient images to remove head tilt in the transverse and coronal plane. Use a sagittal slice just off the midline to align the inferior frontal and inferior occipital poles in the horizontal plane.

Select and Adjust the Color Scale

To create a visual threshold for positivity:

- Draw a region of interest around the cerebellum in the transverse plane.
- Select the plane to go through the cerebellum at the maximum cross-sectional area of the cerebellum.
- Record the mean activity or cerebellar counts (MCC). The region of interest should be drawn with the scan in gray scale and in the transverse plane as seen in the example in Figure 1.

Figure 1: Example of Cerebellar Region of Interest

- Select a color scale for image display that has a rapid transition between two distinct colors in the general range of 25% to 60% of maximum intensity.
- Set the upper contrast value (UCV) of the color scale. Use the following formula to set the visual threshold of 1.65 x MCC to match the rapid transition in the color scale:

UCV = (MCC x 1.65) x (100% / % level of color transition)

If additional guidance on image display is needed, refer to the TAUVID User Guide for PET Image Display available by request from the manufacturer.

2.5 Preparation for Image Interpretation

- Before interpreting the image, review the brain to determine the lobar anatomy. Interpret the images by first evaluating the temporal lobes, followed by occipital, parietal, and frontal lobes bilaterally.
- To evaluate the temporal lobes, subdivide them into four quadrants by placing the horizontal crosshair immediately posterior to the brainstem nuclei and then scrolling inferiorly to place the vertical crosshair through the widest portion of the temporal pole, thus obtaining the anterolateral temporal (ALT), anterior mesial temporal (AMT), posterolateral temporal (PLT) and posterior mesial temporal (PMT) quadrants. See Figure 2 for an example (the left and right image panels show the same scan in two different color scales).

Figure 2: Temporal Lobe Quadrants

2.6 Image Interpretation

Interpret TAUVID imaging independently of the patient's clinical features and other imaging.

Interpret the PET TAUVID images based upon the pattern and density of the radioactive signal within the neocortical gray matter (not within white matter or in regions outside of the brain). Only uptake of tracer in the neocortical grey matter regions should contribute to scan interpretation.

Off-target binding may be seen in the choroid plexus, striatum, and brainstem nuclei. Small foci of noncontiguous tracer uptake may lead to false positive interpretation. Interpret scans that have isolated or noncontiguous, small foci in any region with caution. Some scans may be difficult to interpret due to image noise or motion artifact. For cases where there is uncertainty as to the location of neocortical uptake, use co-registered anatomical imaging to improve localization of uptake.

Positive TAUVID Scan

A positive scan shows increased neocortical activity in posterolateral temporal (PLT), occipital, or parietal/precuneus region(s), with or without frontal activity. Neocortical activity in either hemisphere can contribute to identification of the positive pattern. A positive scan supports the presence of widely distributed tau neuropathology (B3 tau pathology). See Figure 3 for examples (the left and right image panels show the same scans in two different color scales) [see Warnings and Precautions (5.1)].

Negative TAUVID Scan

A negative scan shows no increased neocortical activity, or shows increased neocortical activity isolated to the mesial temporal, anterolateral temporal, and/or frontal regions. See Figure 4 for examples (the left and right image panels show the same scans in two different color scales) [see Warnings and Precautions (5.1)].

Figure 3: Positive Scan Examples

A: Off target binding in the striatum.

Row 1: Example of a patient with increased uptake in PLT.

Row 2: Example of a patient with increased uptake in PLT and occipital regions.

Rows 3 and 4: Example of a patient with increased neocortical activity in PLT, occipital lobe (solid arrows) and precuneus (dashed arrows) (row 3: level of temporal lobes, row 4: level of parietal/precuneus).

Row 5: Example of a patient with increased neocortical activity in medial prefrontal/cingulate, lateral prefrontal, PLT, parietal, occipital and precuneus regions.

Figure 4: Negative Scan Examples

B: Off target binding in the choroid plexus or brainstem nuclei.

Row 1: Example of a patient with no increased neocortical activity (activity is similar in intensity to cerebellar reference region).

Row 2: Example of a patient with increased activity isolated to MTL.

Row 3: Example of a patient with increased neocortical activity isolated to frontal lobe.

Row 4: Example of a patient with small isolated foci of non-contiguous and variable uptake in the PLT (solid arrows); increased activity in the ALT (dashed arrows). This pattern may also be seen in the occipital or parietal region.

2.7 Radiation Dosimetry

Radiation absorbed dose estimates are shown in Table 1 for organs and tissues of adults from intravenous administration of TAUVID. The effective radiation dose resulting from administration of 370 MBq (10 mCi) of TAUVID to an adult weighing 70 kg is estimated to be 8.7 mSv. Critical organs include the upper large intestinal wall, small intestine, and liver. When PET/CT is performed, exposure to radiation will increase in an amount dependent on the settings used in the CT acquisition.

Table 1: Estimated Radiation Absorbed Dose After a TAUVID Injection
Organ/Tissue | Mean Absorbed Dose Per Unit Administered Activity (μGy/MBq)
Adrenal glands | 14
Brain | 8
Breasts | 7
Gallbladder wall | 38
Lower large intestine wall | 35
Small intestine wall | 85
Stomach wall | 13
Upper large intestine wall | 96
Heart wall | 30
Kidneys | 40
Liver | 57
Lungs | 34
Muscle | 9
Ovaries | 21
Pancreas | 14
Red bone marrow | 10
Osteogenic cells | 12
Skin | 6
Spleen | 10
Testes | 7
Thymus gland | 9
Thyroid | 7
Urinary bladder wall | 38
Uterus | 18
Total body | 12
Effective dose (μSv/MBq)a | 24
a Assumed radiation weighting factor, wr, (formerly defined as quality factor, Q) of 1 for conversion of absorbed dose (Gray or rads) to dose equivalent (Sieverts or rem) for F 18. To obtain radiation absorbed dose in rad/mCi from above table, multiply the dose in μGy/MBq by 0.0037 (e.g., 14 μGy/MBq x 0.0037 = 0.0518 rad/mCi).

3 DOSAGE FORMS AND STRENGTHS

Injection: clear, colorless solution in a 50 mL or 100 mL multiple-dose vial containing 300 MBq/mL to 3,700 MBq/mL (8.1 mCi/mL to 100 mCi/mL) flortaucipir F 18 at the end of synthesis.

4 CONTRAINDICATIONS

None.

5 WARNINGS AND PRECAUTIONS

5.1 Risk of Misdiagnosis in Patients Evaluated for Alzheimer's disease

TAUVID does not target β-amyloid, one of two required components of the neuropathological diagnosis of AD.

TAUVID performance for detecting tau pathology was assessed in terminally ill patients, the majority of whom had AD dementia with B3 level NFT pathology. TAUVID performance for detecting tau pathology may be lower in patients in earlier stages of the pathological spectrum [see Clinical Studies (14)].

Negative TAUVID Scan

NFTs may be present at levels that qualify for the neuropathological diagnosis of AD (B2 tau pathology in the presence of at least moderate levels of cortical amyloid pathology) in patients with a negative TAUVID scan. Consider additional evaluation to confirm the absence of AD pathology in patients with a negative TAUVID scan.

False Positive TAUVID Scan

Small foci of noncontiguous tracer uptake may lead to a false positive TAUVID scan. Only uptake of tracer in the neocortex should contribute to the interpretation of a positive TAUVID scan [see Dosage and Administration (2.4)].

5.2 Risk of Chronic Traumatic Encephalopathy Misdiagnosis

The safety and effectiveness of TAUVID have not been established for patients being evaluated for CTE. Preliminary non-clinical and clinical investigations suggest differences in tau conformation and distribution may limit flortaucipir F 18 binding. Therefore, TAUVID is not indicated for detection of CTE.

5.3 Radiation Risk

Diagnostic radiopharmaceuticals, including TAUVID, expose patients to radiation [see Dosage and Administration (2.7)]. Radiation exposure is associated with a dose-dependent increased risk of cancer. Ensure safe handling and preparation procedures to protect patients and health care workers from unintentional radiation exposure [see Dosage and Administration (2.1, 2.2)].

6 ADVERSE REACTIONS

6.1 Clinical Trials Experience

Because clinical trials are conducted under widely varying conditions, adverse reaction rates observed in the clinical trials of a drug cannot be directly compared to rates in the clinical trials of another drug and may not reflect the rates observed in practice.

In clinical studies, 1,921 study participants were exposed to TAUVID [see Clinical Studies (14)]. In these studies, 885 study participants received 240 MBq of TAUVID (about 65% of the recommended dose) and 1,036 study participants received 370 MBq of TAUVID (the recommended dose). The adverse reactions reported in ≥ 0.5% of study participants are shown in Table 2.

Table 2: Adverse Reactions with a Frequency ≥0.5% in Adults Who Received TAUVID in Clinical Trials (n = 1,921)
Adverse Reaction | n (%)
Headache | 26 (1.4%)
Injection site pain | 23 (1.2%)
Increased blood pressure | 15 (0.8%)

Adverse reactions with a frequency <0.5% in adults who received TAUVID in clinical trials include:

Nervous system disorders: dysgeusia

8 USE IN SPECIFIC POPULATIONS

8.1 Pregnancy

Risk Summary

All radiopharmaceuticals, including TAUVID, have the potential to cause fetal harm depending on the fetal stage of development and the magnitude of radiation dose. Advise a pregnant woman of the potential risks of fetal exposure to radiation doses with administration of TAUVID. TAUVID is not likely to be used in females of reproductive age.

There are no available data on TAUVID use in pregnant women. No animal reproduction studies using flortaucipir F 18 have been conducted to evaluate its effect on female reproduction and embryo-fetal development.

The estimated background risk of major birth defects and miscarriage for the indicated population is unknown. All pregnancies have a background risk of birth defect, loss, or other adverse outcomes. In the U.S. general population, the estimated background risk of major birth defects and miscarriage in clinically recognized pregnancies is 2 to 4% and 15 to 20%, respectively.

8.2 Lactation

Risk Summary

There are no data on the presence of flortaucipir F 18 in human milk, or its effects on the breastfed infant or milk production. Lactation studies have not been conducted in animals. Advise a lactating woman to avoid breastfeeding for 4 hours after TAUVID administration in order to minimize radiation exposure to a breastfed infant.

8.4 Pediatric Use

The safety and effectiveness of TAUVID in pediatric patients have not been established.

8.5 Geriatric Use

Of 1,921 study participants in completed clinical studies of TAUVID, 1,544 (80%) TAUVID-treated subjects were ≥ 65 years old, while 839 (44%) were ≥ 75 years old. No overall differences in safety or effectiveness of TAUVID were observed between subjects ≥ 65 years old and younger adult subjects, and other reported clinical experience has not identified differences in safety or effectiveness between elderly and younger patients.

11 DESCRIPTION

11.1 Chemical Characteristics

TAUVID contains flortaucipir fluorine 18 (F 18). Chemically, flortaucipir F 18 is 7-(6-[F-18]fluoropyridin-3-yl)-5H-pyrido[4,3-b]indole. The molecular weight is 262.27, the molecular formula is C16H10[^18F]N3, and the structural formula is:

TAUVID is a sterile, non-pyrogenic solution for intravenous injection. The clear, colorless solution free of visible particulate matter is supplied ready to use, and each milliliter contains up to 2 micrograms of flortaucipir and 300 to 3,700 MBq (8.1 to 100 mCi) flortaucipir F 18 at end of synthesis, 1.5 mg of L-cysteine hydrochloride monohydrate USP, 2.1 mg of dibasic sodium phosphate anhydrous USP, up to 55 of micrograms hydrogen chloride and 0.1 mL dehydrated alcohol in 0.9% sodium chloride injection USP. The pH of the solution is between 5.5 and 7.5.

11.2 Physical Characteristics

TAUVID is radiolabeled with fluorine 18 (F 18), a cyclotron produced radionuclide that decays by positron emission to stable oxygen 18 with a half-life of 109.8 minutes. The principal photons useful for diagnostic imaging are the coincident pair of 511 keV gamma photons, resulting from the interaction of the emitted positron with an electron (Table 3).

Table 3: Principal Radiation Produced from Decay of Fluorine 18
Radiation | Energy Level (keV) | Abundance (%)
Positron | 249.8 | 96.9
Gamma | 511 | 193.5

11.3 External Radiation

The point source air-kerma coefficient for F18 is 3.74E^-17 Gy m^2/(Bq s). The first half-value thickness of lead (Pb) for F 18 gamma rays is approximately 6 mm. The relative reduction of radiation emitted by F 18 that results from various thicknesses of lead shielding is shown in Table 4. The use of 8 cm of Pb will decrease the radiation transmission (i.e., exposure) by a factor of about 10,000.

Table 4: Radiation Attenuation of 511 keV Gamma Rays by Lead Shielding
Shield Thickness cm of lead (Pb) | Coefficient of Attenuation
0.6 | 0.5
2 | 0.1
4 | 0.01
6 | 0.001
8 | 0.0001

12 CLINICAL PHARMACOLOGY

12.1 Mechanism of Action

Flortaucipir F 18 binds to aggregated tau protein. In the brains of patients with AD, tau aggregates combine to form NFTs, one of two components required for the neuropathological diagnosis of AD. In vitro, flortaucipir F 18 binds to paired helical filament (PHF) tau purified from brain homogenates of donors with AD. The dissociation constant (Kd) of flortaucipir F 18 binding to PHFs is 0.57 nM. In vivo, flortaucipir F 18 is differentially retained in neocortical areas that contain aggregated tau. In vitro, tritiated flortaucipir has been reported to bind with low nanomolar affinity to monoamine oxidase-A and monoamine oxidase-B, which could contribute to off target binding.

12.2 Pharmacodynamics

The relationship between flortaucipir F 18 plasma concentrations and image interpretation was not explored in clinical trials.

Effect of MAO Inhibitors on Flortaucipir Binding in AD Patients

TAUVID PET signal was slightly reduced by rasagiline, a MAO-B inhibitor, in vivo in low tau, high MAO-B areas of the brain such as the nucleus accumbens, putamen, and caudate. However, there is little potential for MAO binding to affect TAUVID scan interpretation in neocortical areas.

12.3 Pharmacokinetics

After intravenous administration of TAUVID, flortaucipir F 18 was distributed throughout the body with less than 10% of the injected F 18 radioactivity present in the blood by 5 minutes following administration, and less than 5% present in the blood by 10 minutes after administration. The residual F 18 in circulation during the 80-minute to 100-minute imaging window was approximately 28% to 34% parent, with the remainder being metabolites.

Clearance occurs primarily by hepatobiliary and renal excretion.

13 NONCLINICAL TOXICOLOGY

13.1 Carcinogenesis, Mutagenesis, Impairment of Fertility

Animal studies to assess the carcinogenicity or reproductive toxicity potentials of flortaucipir F 18 have not been conducted.

In an in vitro bacterial reverse mutation assay (Ames test), increases in the number of revertant colonies were observed in 4 of the 5 strains exposed to flortaucipir F 19. In a chromosomal aberration in vitro study with Chinese hamster ovary (CHO) cells, flortaucipir F 19 increased the percent of cells with structural aberrations with 3 hour exposure with or without S9 metabolic activation. Twenty hour exposure without activation produced an increase in structural aberrations at all tested concentrations.

Flortaucipir F 19 was evaluated in a rat micronucleus study and showed no genotoxicity. In this study, flortaucipir F 19 did not increase the number of micronucleated polychromatic erythrocytes at the highest achievable dose level, 1600 μg/kg/day, when given for two consecutive days.

14 CLINICAL STUDIES

The performance of TAUVID imaging to estimate the density and distribution of aggregated tau neurofibrillary tangles (NFTs) was evaluated in two clinical studies: Study 1 (NCT02516046) and Study 2 (NCT03901092). In each study, TAUVID imaging was interpreted by 5 independent readers who were blinded to clinical information. Readers interpreted TAUVID imaging as positive or negative [see Dosage and Administration (2.6)].

Study 1 enrolled 156 terminally ill patients who agreed to undergo TAUVID imaging and to participate in a postmortem brain donation program. In 64 of these patients, reader interpretation of the TAUVID scan was compared to tau pathology based on scoring provided by independent pathologists, who evaluated the density and distribution of NFTs in the post-mortem brain (see Table 5). Of the 64 patients, the mean age was 83 years (range 55 to 100); 34 were female; 49 had dementia, 1 had mild cognitive impairment, and 14 had no cognitive impairment on clinical evaluation around the time of TAUVID imaging.

Table 5: Study 1 Tau Pathology Scoring
Tau Pathology Score | Distribution of Tau NFTs in the Brain
B0 | No NFTs
B1 | NFTs limited to transentorhinal brain region
B2 | B1 + NFTs limited to limbic brain regions
B3 | B2 + NFTs distributed throughout the neocortex

Image reader performance for distinguishing B3 (positive) from B0-B2 (negative) tau pathology is shown in Table 6.

Table 6: Study 1 TAUVID Scan Reader Performance for B3 Tau Pathology
Reader | True Positive | True Negative | False Positive | False Negative | Sensitivity % (95% CIa) | Specificity % (95% CI)
1 | 38 | 17 | 8 | 1 | 97 (87, 100) | 68 (48, 83)
2 | 36 | 23 | 2 | 3 | 92 (80, 97) | 92 (75, 98)
3 | 36 | 22 | 3 | 3 | 92 (80, 97) | 88 (70, 96)
4 | 36 | 19 | 6 | 3 | 92 (80, 97) | 76 (57, 89)
5 | 39 | 13 | 12 | 0 | 100 (91, 100) | 52 (34, 70)
a CI = confidence interval.

The performance of the five TAUVID readers for sensitivity (95% CI) ranged from 92% (80, 97) to 100% (91, 100) and for specificity (95% CI) ranged from 52% (34, 70) to 92% (75, 98). Exploratory analysis evaluated how the same TAUVID interpretations distinguished B2-B3 from B0-B1 tau pathology, a threshold used in integrating tau and amyloid pathology for the neuropathological diagnosis of AD. In this analysis, the performance of the five TAUVID readers for sensitivity (95% CI) ranged from 68% (55, 79) to 86% (74, 93) and for specificity (95% CI) ranged from 63% (31, 86) to 100% (68, 100) [see Warnings and Precautions (5.1)].

Study 2 included the same terminally ill patients as in Study 1 (plus 18 additional terminally ill patients) and 159 patients with cognitive impairment being evaluated for AD (the indicated population). Inter-reader agreement for five new TAUVID readers was evaluated using Fleiss' kappa statistic (95% CI) and found to be 0.87 (0.83, 0.91) across all 241 patients. Exploratory analysis evaluated inter-reader agreement in two subgroups. In this analysis, Fleiss' kappa (95% CI) was 0.82 (0.75, 0.88) in the terminally ill patients and 0.90 (0.85, 0.95) in the indicated population.

16 HOW SUPPLIED/STORAGE AND HANDLING

16.1 How Supplied

TAUVID injection is supplied in a 50 mL or 100 mL multiple-dose vial containing a clear, colorless solution free of visible particulate matter at a strength of 300 MBq/mL to 3,700 MBq/mL (8.1 mCi/mL to 100 mCi/mL) flortaucipir F 18 at end of synthesis. Each vial contains multiple doses and is enclosed in a shield container to minimize external radiation exposure.

50 mL | NDC 0002-1220-50 (IC1220)
100 mL | NDC 0002-1220-48 (IC1220)

16.2 Storage and Handling

Storage

Store TAUVID at 25°C (77°F); excursions permitted to 15°C to 30°C (59°F to 86°F) [see USP Controlled Room Temperature]. TAUVID does not contain a preservative. Store TAUVID upright in a shielding container [see Dosage and Administration (2.1)]. The expiration date and time are provided on the container label. Use TAUVID within the labeled expiration.

Handling

This preparation is approved for use by persons under license by the Nuclear Regulatory Commission or the relevant regulatory authority of an Agreement State.

17 PATIENT COUNSELING INFORMATION

Radiation Risk

Advise patients of the radiation risk of TAUVID [see Warnings and Precautions (5.3)].

Pregnancy

Advise a pregnant woman of the potential risks of fetal exposure to radiation doses with TAUVID [see Use in Specific Populations (8.1)].

Lactation

Advise a lactating woman to avoid breastfeeding for 4 hours after TAUVID administration in order to minimize radiation exposure to a breastfed infant [see Use in Specific Populations (8.2)].

Manufactured for Avid Radiopharmaceuticals, a wholly-owned subsidiary of Eli Lilly and Company, Philadelphia, PA 19104

Copyright © 2020, 2024, Eli Lilly and Company. All rights reserved.

TAU-0003-USPI-20240205

PACKAGE LABEL – Tauvid 100 mci 50 mL SHIELD

NDC 0002-1220-50

Tauvid™

Flortaucipir F 18 Injection

50 mL Multiple-Dose Vial

Sterile

Rx Only

CAUTION ☢ RADIOACTIVE MATERIAL

300 MBq/mL to 3,700 MBq/mL (8.1 mCi/mL to 100 mCi/mL) at End of Synthesis

For Intravenous Use Only

_____MBq (_____mCi) in _____mL at _____:_____ on _____

Expires at _____:_____ on _____

Batch No._____

Dosage: See prescribing information.

Contains up to 2 micrograms of flortaucipir, 1.5 mg L-cysteine hydrochloride monohydrate USP, 2.1 mg of dibasic sodium phosphate anhydrous USP, up to 55 micrograms of hydrogen chloride and 0.1 mL dehydrated alcohol USP in 0.9% sodium chloride injection USP per milliliter of solution. Store vial upright in a shielding container at 25°C (77°F); excursions permitted to 15°C to 30°C (59°F to 86°F).

Manufactured by PETNET Solutions, Inc. Knoxville, TN 37932 for Avid Radiopharmaceuticals, a wholly-owned subsidiary of Eli Lilly and Company, Philadelphia, PA 19104